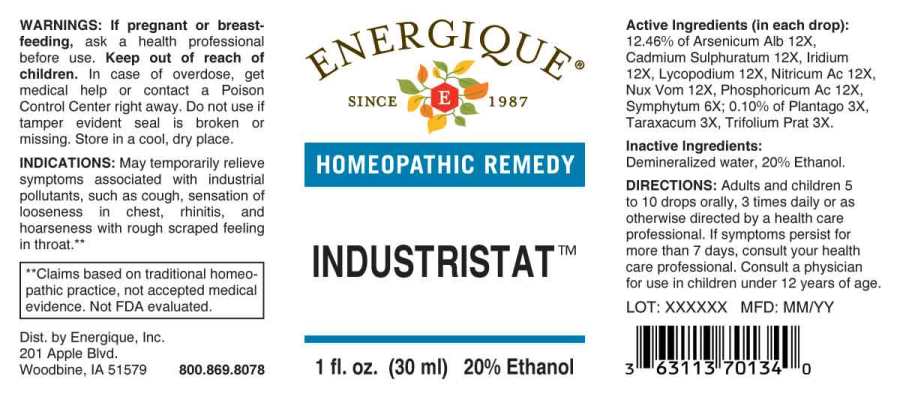 DRUG LABEL: Industristat
NDC: 44911-0442 | Form: LIQUID
Manufacturer: Energique, Inc.
Category: homeopathic | Type: HUMAN OTC DRUG LABEL
Date: 20241028

ACTIVE INGREDIENTS: PLANTAGO MAJOR WHOLE 3 [hp_X]/1 mL; TARAXACUM OFFICINALE 3 [hp_X]/1 mL; TRIFOLIUM PRATENSE FLOWER 3 [hp_X]/1 mL; COMFREY ROOT 6 [hp_X]/1 mL; ARSENIC TRIOXIDE 12 [hp_X]/1 mL; CADMIUM SULFIDE 12 [hp_X]/1 mL; IRIDIUM 12 [hp_X]/1 mL; LYCOPODIUM CLAVATUM SPORE 12 [hp_X]/1 mL; NITRIC ACID 12 [hp_X]/1 mL; STRYCHNOS NUX-VOMICA SEED 12 [hp_X]/1 mL; PHOSPHORIC ACID 12 [hp_X]/1 mL
INACTIVE INGREDIENTS: WATER; ALCOHOL

DRUG FACTS:

ACTIVE INGREDIENTS:

(in each drop): 12.46% of Arsenicum Album 12X, Cadmium Sulphuratum 12X, Iridium Metallicum 12X, Lycopodium Clavatum 12X, Nitricum Acidum 12X, Nux Vomica 12X, Phosphoricum Acidum 12X, Symphytum Officinale 6X; 0.10% of Plantago Major 3X, Taraxacum Officinale 3X, Trifolium Pratense 3X.

INDICATIONS:

May temporarily relieve symptoms associated with industrial pollutants, such as cough, sensation of looseness in chest, rhinitis, and hoarseness with rough scraped feeling in the throat.**

**Claims based on traditional homeopathic practice, not accepted medical evidence. Not FDA evaluated.

WARNINGS:

If pregnant or breast-feeding, ask a health professional before use.

Keep out of reach of children. In case of overdose, get medical help or contact a Poison Control Center right away.

Do not use if tamper evident seal is broken or missing. Store in a cool, dry place.

Keep out of reach of children. In case of overdose, get medical help or contact a Poison Control Center right away.

DIRECTIONS:

Adults and children 5 to 10 drops orally, 3 times daily or as otherwise directed by a health care professional. If symptoms persist for more than 7 days, consult your health care professional.

Consult a physician for use in children under 12 years of age.

INDICATIONS:

May temporarily relieve symptoms associated with industrial pollutants, such as cough, sensation of looseness in chest, rhinitis, and hoarseness with rough scraped feeling in the throat.**

**Claims based on traditional homeopathic practice, not accepted medical evidence. Not FDA evaluated.

INACTIVE INGREDIENTS:

Demineralized water, 20% Ethanol.

QUESTIONS:

Dist. by Energique, Inc.

201 Apple Blvd

Woodbine, IA 51579 800.869.8078

PACKAGE LABEL DISPLAY:

ENERGIQUE

SINCE 1987

HOMEOPATHIC REMEDY

INDUSTRISTAT

1 fl. oz. (30 ml)